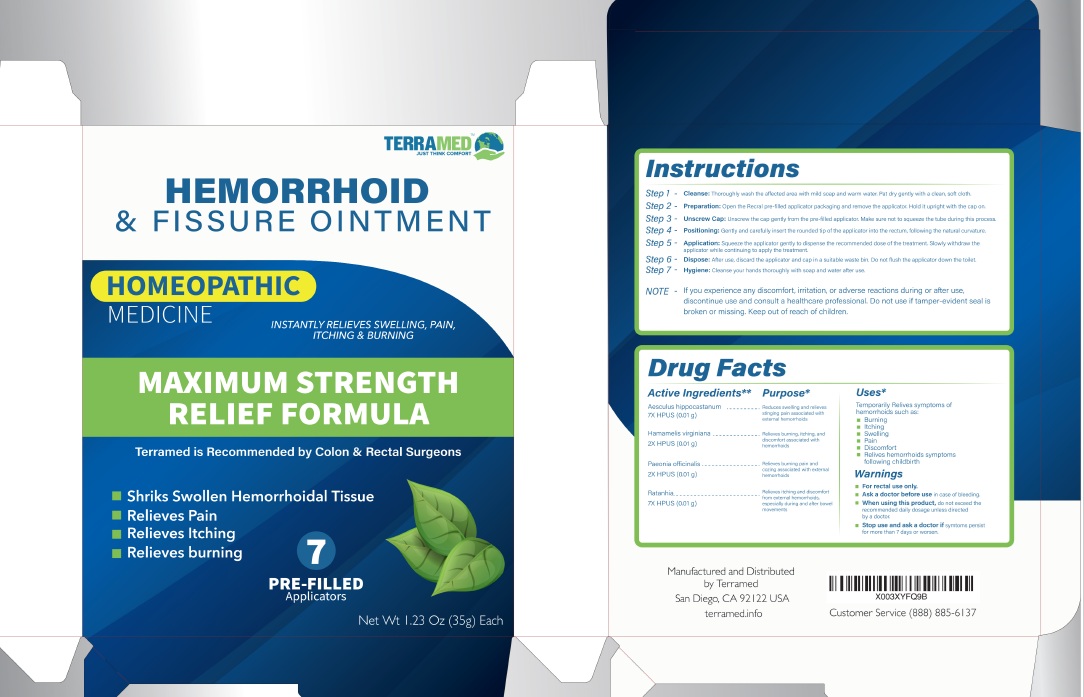 DRUG LABEL: Terramed Just Think Comfort Hemorrhoid Fissure Treatment
NDC: 83004-021 | Form: OINTMENT
Manufacturer: Rida LLC
Category: homeopathic | Type: HUMAN OTC DRUG LABEL
Date: 20250320

ACTIVE INGREDIENTS: HORSE CHESTNUT 7 [hp_X]/35 g; HAMAMELIS VIRGINIANA LEAF WATER 2 [hp_X]/35 g; PAEONIA OFFICINALIS WHOLE 2 [hp_X]/35 g; KRAMERIA LAPPACEA ROOT 7 [hp_X]/35 g
INACTIVE INGREDIENTS: LANOLIN; GLYCERYL MONOSTEARATE; PETROLATUM; CETOSTEARYL ALCOHOL; HYDROGENATED CASTOR OIL; GLYCERIN; MENTHOL, UNSPECIFIED FORM; EUCALYPTUS OIL; TEA TREE OIL; LINALOOL, (+)-

Active Ingredient

Aesculus hippocastanum 7X HPUS (0.01 g)........................Reduces swelling and relieves stinging pain associated with external hemorrhoids

Hamamelis virginiana 2X HPUS (0.01 g)............................................Relieves burning, itching, and discomfort associated with hemorrhoids

Paeonia officinalis (Peony) 2X H PUS (0.01 g)........................................Relieves burning pain and cozing associated with external hemorrhoids

Ratanhia 7X HPUS (0.01 g)................................................................Relieves itching and discomfort from external hemorrhoids,

especially during and after bowel movements

Uses

Temporarily Relives symptoms of hemorrhoids such as:
• Burning
• Itching
• Swelling
• Pain
• Discomfort
• Relives hemorrhoids symptoms
following childbirth

Warnings

- For rectal use only.
- Ask a doctor before usein case of bleeding.
- When using this product, do not exceed the recommended daily dosage unless directed by a doctor.
- Stop use and ask a doctor ifsymtoms persist for more than 7 days or worsen.

Directions

Step 1 - Cleanse: Thoroughly wash the affected area with mild soap and warm water. Pat dry gently with a clean, soft cloth.

Step 2 - Preparation: Open the Recral pre-filled applicator packaging and remove the applicator. Hold it upright with the cap on.

Step 3- Unscrew Cap: Unscrew the cap gently from the pre-filled applicator. Make sure not to squeeze the tube during this process.

Step 4- Positioning: Gently and carefully insert the rounded tip of the applicator into the rectum, following the natural curvature.

Step 5- Application: Squeeze the applicator gently to dispense the recommended dose of the treatment. Slowly withdraw the applicator

while continuing to apply the treatment.

Step 6 - Dispose: After use, discard the applicator and cap in a suitable waste bin. Do not flush the applicator down the toilet.

Step 7 - Hygiene: Cleanse your hands thoroughly with soap and water after use.

Other Information

If you experience any discomfort, irritation, or adverse reactions during or after use, discontinue use and consult a healthcare professional. Do not use if tamper-evident seal is broken or missing. Keep out of reach of children.

Inactive ingredients

Lanolin, Glyceryl Stearate, Petrolatum, Cetearyl Alcohol, Hydrogenated Castor Oil, Glycerin, Menthol, Eucalyptus Globulus (Eucalyptus) Oil, Tea Tree Oil, Linalool